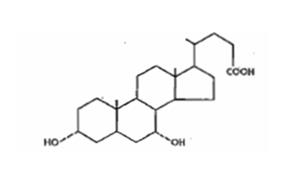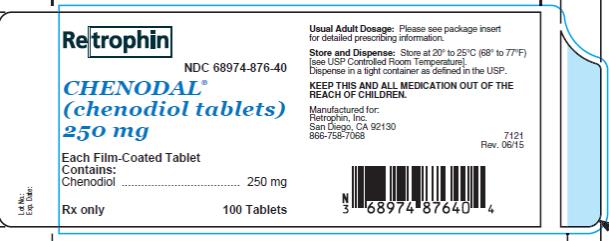 DRUG LABEL: Chenodal
NDC: 68974-876 | Form: TABLET, FILM COATED
Manufacturer: Travere Therapeutics
Category: prescription | Type: HUMAN PRESCRIPTION DRUG LABEL
Date: 20251212

ACTIVE INGREDIENTS: CHENODIOL 250 mg/1 1
INACTIVE INGREDIENTS: SILICON DIOXIDE; CELLULOSE, MICROCRYSTALLINE; SODIUM STARCH GLYCOLATE TYPE A POTATO; MAGNESIUM STEARATE; METHYLCELLULOSE (100 MPA.S); GLYCERIN; SODIUM LAURYL SULFATE

Chenodal

CHENODAL® (CHENODIOL TABLETS) 250 MG

SPECIAL NOTE

Because of the potential hepatoxicity of chenodiol, poor response rate in some subgroups of chenodiol treated patients, and an increased rate of a need for cholecystectomy in other chenodiol treated subgroups, chenodiol is not an appropriate treatment for many patients with gallstones. Chenodiol should be reserved for carefully selected patients and treatment must be accompanied by systematic monitoring for liver function alterations. Aspects of patient selection, response rates and risks versus benefits are given in the insert.

DESCRIPTION

Chenodiol is the non-proprietary name for chenodeoxycholic acid, a naturally occurring human bile acid. It is a bitter-tasting white powder consisting of crystalline and amorphous particles freely soluble in methanol, acetone and acetic acid and practically insoluble in water. Its chemical name is 3α, 7α-dihydroxy-5β-cholan-24-oic acid (C24H40O4), it has a molecular weight of 392.58, and its structure is shown below;

Chenodiol film-coated tablets for oral administration contain 250 mg of chenodiol.

Inactive ingredients: pregelatinized starch; silicon dioxide; microcrystalline cellulose, sodium starch glycollate; and magnesium stearate; the thin-film coating contains: opadry YS-2-7035 [consisting of methylcellulose and glycerin] and sodium lauryl sulfate

CLINICAL PHARMACOLOGY

At therapeutic doses, chenodiol suppresses hepatic synthesis of both cholesterol and cholic acid, gradually replacing the latter and its metabolite, deoxycholic acid in an expanded bile acid pool. These actions contribute to biliary cholesterol desaturation and gradual dissolution of radiolucent cholesterol gallstones in the presence of a gall-bladder visualized by oral cholecystography. Chenodiol has no effect on radiopaque (calcified) gallstones or on radiolucent bile pigment stones.

Chenodiol is well absorbed from the small intestine and taken up by the liver where it is converted to its taurine and glycine conjugates and secreted in bile. Owing to 60 % to 80% first-pass hepatic clearance, the body pool of chenodiol resides mainly in the enterohepatic circulation; serum and urinary bile acid levels are not significantly affected during chenodiol therapy.

At steady-state, an amount of chenodiol near the daily dose escapes to the colon and is converted by bacterial action to lithocholic acid. About 80% of the lithocholate is excreted in the feces; the remainder is absorbed and converted in the liver to its poorly absorbed sulfolithocholyl conjugates. During chenodiol therapy there is only a minor increase in biliary lithocholate, while fecal bile acids are increased three- to fourfold.

Chenodiol is unequivocally hepatotoxic in many animal species, including sub-human primates at doses close to the human dose. Although the theoretical cause is the metabolite, lithocholic acid, an established hepatotoxin, and man has an efficient mechanism for sulfating and eliminating this substance, there is some evidence that the demonstrated hepatotoxicity is partly due to chenodiol per se. The hepatotoxicity of lithocholic acid is characterized biochemically and morphologically as cholestatic.

Man has the capacity to form sulfate conjugates of lithocholic acid. Variation in this capacity among individuals has not been well established and a recent published report suggests that patients who develop chenodiol-induced serum aminotransferase elevations are poor sulfators of lithocholic acid (see ADVERSE REACTIONS and WARNINGS).

General Clinical Results:

Both the desaturation of bile and the clinical dissolution of cholesterol gallstones are dose-related. In the National Cooperative Gallstone Study (NCGS) involving 305 patients in each treatment group, placebo and chenodiol dosages of 375 mg and 750 mg per day were associated with complete stone dissolution in 0.8%, 5.2% and 13.5%, respectively, of enrolled subjects over 24 months of treatment. Uncontrolled clinical trials using higher doses than those used in the NCGS have shown complete dissolution rates of 28 to 38% of enrolled patients receiving body weight doses of from 13 to 16 mg/kg/day for up to 24 months. In a prospective trial using 15 mg/kg/day, 31% enrolled surgical-risk patients treated more than six months (n = 86) achieved complete confirmed dissolutions.

Observed stone dissolution rates achieved with chenodiol treatment are higher in subgroups having certain pretreatment characteristics. In the NCGS, patients with small {less than 15 mm in diameter} radiolucent stones, the observed rate of complete dissolution was approximately 20% on 750 mg/day. In the uncontrolled trails using 13 to 16 mg/kg/day doses of chenodiol, the rates of complete dissolution for small radiolucent stones ranged from 42% to 60%. Even higher dissolution rates have been observed in patients with small floatable stones. (See Floatable versus Nonfloatable Stones,below). Some obese patients and occasional normal weight patients fail to achieve bile desaturation even with doses of chenodiol up to 19 mg/kg/day for unknown reasons. Although dissolution is generally higher with increased dosage of chenodiol, doses that are too low are associated with increased cholecystectomy rates (see ADVERSE REACTIONS).

Stones have recurred within five years in about 50% of patients following complete confirmed dissolutions. Although retreatment with chenodiol has proven successful in dissolving some newly formed stones, the indications for and safety of retreatment are not well defined. Serum aminotransferase elevations and diarrhea have been notable in all clinical trials and are dose-related (refer to ADVERSE REACTIONSand WARNINGS sections for full information).

Floatable versus Nonfloatable Stones

A major finding in clinical trials was a difference between floatable and nonfloatable stones, with respect to both natural history and response to chenodiol. Over the two-year course of the National Cooperative Gallstone Study (NCGS), placebo – treated patients with floatable stones (n = 47) had significantly higher rates of biliary pain and cholecystectomy than patients with nonfloatable stones (n = 258) (47% versus 27% and 19%versus 4%, respectively). Chenodiol treatment (750 mg/day) compared to placebo was associated with a significant reduction in both biliary pain and the cholecystectomy rates in the group with floatable stones (27% versus 47% and 1.5% versus 19%, respectively). In an uncontrolled clinical trial using 15 mg/kg/day, 70% of the patients with small (less than 15 mm) floatable stones (n = 10) had complete confirmed dissolution.

In the NCGS in patients with nonfloatable stones, chenodiol produced no reduction in biliary pain and showed a tendency to increase the cholecystectomy rate (8% versus 4%). This finding was more pronounced with doses of chenodiol below 10 mg/kg. The subgroup of patients with nonfloatable stones and a history of biliary pain had the highest rates of cholecystectomy and aminotransferase elevations during chenodiol treatment. Except for the NCGS subgroup with pretreatment biliary pain, dose-related aminotransferase elevations and diarrhea have occurred with equal frequency in patients with floatable or nonfloatable stones. In the uncontrolled clinical trial mentioned above, 27% of the patients with nonfloatable stones (n = 59) had complete confirmed dissolutions, including 35% with small (less than 15 mm)(n= 40) and only 11% with large, nonfloatable stones (n= 19).

Of 916 patients enrolled NCGS, 17.6% had stones seen in upright form (horizontal X-ray beam) to float in the dye-laden bile during oral cholecystography using iopanoic acid. Other investigators report similar findings. Floatable stones are not detected by ultrasonography in the absence for dye. Chemical analysis has shown floatable stones to be essentially pure cholesterol).

Other Radiographic and Laboratory Features:Radiolucent stones may have rims or centers of opacity representing calcification. Pigment stones and partially calcified radiolucent stones do not respond to chenodiol. Subtle calcification can sometimes be detected in flat film X-rays, if not obvious in the oral cholecystogram. Among nonfloatable stones, cholesterol stones are more apt than pigment stones to be smooth surfaced, less than 0.5 cm in diameter, and to occur in numbers less than 10. As stone size number and volume increase, the probability of dissolution within 24 months decreases. Hemolytic disorders, chronic alcoholism, biliary cirrhosis and bacterial invasion of the biliary system predispose to pigment gallstone formation. Pigment stones of primary biliary cirrhosis should be suspected in patients with elevated alkaline phosphates, especially if positive anti-mitochondrial antibodies are present. The presence of microscopic cholesterol crystals in aspirated gallbladder bile, and demonstration of cholesterol super saturation by bile lipid analysis increase the likelihood that the stones are cholesterol stones.

PATIENT SELECTION

Evaluation of Surgical Risk;Surgery offers the advantage of immediate and permanent stone removal, but carries a fairly high risk. In some patients. About 5% of cholecystectomized patients have residual symptoms or retained common duct stones. The spectrum to surgical risk varies as a function of age and the presence of disease other than cholelithiasis. Selected tabulation of results from the National Halothane Study (JAMA, 1968, 197:775-778) is shown below: the study included 27,600 cholecystectomies.

Low Risk Patients* |  | Cholecystectomy | Cholecystectomy & Common Duct Exploration
Women | 0-49 yrs | 1/1851 | 1/469
 | 50-69 yrs | 1/357 | 1/99
Men | 0-49 yrs | 1/981 | 1/243
 | 50-69 yrs | 1/185 | 1/52
High Risk Patients**
Women | 0-49 yrs | 1/79 | 1/21
 | 50-69 yrs | 1/56 | 1/17
Men | 0-49 yrs | 1/41 | 1/11
 | 50-69 yrs | 1/30 | 1/9
* Includes those with good health or moderate systemic disease, with or without emergency surgery. ** Severe or extreme systemic disease, with or with-out emergency surgery.

Women in good health, or having only moderate systemic disease, under 49 years of age have the lowest rate (0.054%); men in all categories have a surgical mortality rate twice that of women; common duct exploration quadruples the rates in all categories; the rates rise with each decade of life and increase tenfold or more in all categories with severe or extreme systemic disease.

Relatively young patients requiring treatment might be better treated by surgery than with Chenodiol, because treatment with chenodiol, even if successful, is associated with a high rate of recurrence, The long-term consequences of repeated courses of chenodiol in terms of liver toxicity, neoplasia and elevated cholesterol levels are not know.

Watchful waiting has the advantage that no therapy may ever be required. For patients with silent or minimally symptomatic stones, the rate of moderate to severe symptoms or gallstone complications is estimated to be between 2% and 6% per year, leading to a cumulative rate of 7% and 27%in five years. Presumably the rate is higher for patients already having symptoms.

INDICATIONS AND USAGE

Chenodiol is indicated for patients with radiolucent stones in well-opacifying gallbladders, in whom selective surgery would be undertaken except for the presence of increased surgical risk due to systemic disease or age. The likelihood of successful dissolution is far greater if the stones are floatable or small. For patients with nonfloatable stones, dissolution is less likely and added weight should be given to the risk that more emergent surgery might result form a delay due to unsuccessful treatment. Safety of use beyond 24 months is not established. Chenodiol will not dissolve calcified (radiopaque) or radiolucent bile pigment stones.

CONTRAINDICATIONS

Chenodiol is contraindicated in the presence of know hepatocyte dysfunction or bile ductal abnormalities such as intrahepatic cholestasis, primary biliary cirrhosis or sclerosing cholangitits (see Warnings); a gallbladder confirmed as nonvisualizing after two consecutive single doses of dye; radiopaque stones; or gallstone complications or compelling reasons for gallbladder surgery including unremitting acute cholecystitis, cholangitis, biliary obstruction, gallstone pancreatitis, or biliary gastrointestinal fistula.

Pregnancy Category X:

Chenodiol may cause fetal harm when administered to a pregnant woman. Serious hepatic, renal and adrenal lesions occurred in fetuses of female Rhesus monkeys given 60 to 90 mg/kg/day (4 to 6 times the maximum recommended human dose, MRHD) from day 21 to day 45 of pregnancy. Hepatic lesions also occurred in neonatal baboons whose mothers had received 18 to 38 mg/kg (1 to 2 times the MRHD), all during pregnancy. Fetal malformations were not observed. Neither fetal liver damage nor fetal abnormalities occurred in reproduction studies in rats and hamsters. No human data are available at this time. Chenodiol is contraindicated in women who are or may become pregnant. If this drug is used during pregnancy, or if the patient becomes pregnant while taking this drug, the patient should be apprised of the potential hazard to the fetus.

WARNINGS

Safe use of chenodiol depends upon selection of patients without pre-existing liver disease and upon faithful monitoring of serum aminotransferase levels to detect drug-induced liver toxicity. Aminotransferase elevations over three times the upper limit of normal have required discontinuation of chenodiol in 2% to 3% of patients. Although clinical and biopsy studies have not shown fulminant lesions, the possibility remains that an occasional patient may develop serious hepatic disease. Three patients with biochemical and histologic pictures of chronic active hepatitis while on chenodiol, 375 mg/day or 750 mg/day, have been reported. The biochemical abnormalities returned spontaneously to normal in two of the patients within 13 and 17 months; and after 17 months’ treatment with prednisone in the third. Follow-up biopsies were not done; and the causal relationship of the drug could not be determined. Another biopsied patient was terminated from therapy because of elevated aminotransferase levels and a liver biopsy was interpreted as showing active drug hepatitis.

One patient with sclerosing cholangitis, biliary cirrhosis and history of jaundice died during chenodiol treatment for hepatic duct stones. Before treatment, serum aminotransferase and alkaline phosphate levels were over twice the upper limit of normal; within one month they rose to over 10 time normal. Chenodiol was discontinued at seven weeks, when the patient was hospitalized with advanced hepatic failure and E. coli peritonitis; death ensued at the eight week. A contribution of chenodiol to the fatal outcome could not be ruled out.

Epidemiologic studies suggest that bile acids might contribute to human colon cancer, but direct evidence is lacking. Bile acids, including chenodiol and lithocholic acid, have no carcinogenic potential in animal models, but have been shown to increase the number of tumors when administered with certain know carcinogens. The possibility that chenodiol therapy might contribute to colon cancer in otherwise susceptible individuals cannot be ruled out.

PRECAUTIONS

Information for Patients

Patients should be counseled on the importance of periodic visits for liver function tests and oral cholecystograms (or ultrasonograms) for monitoring stone dissolution; they should be made aware of the symptoms of gallstone complications and be warned to report immediately such symptoms to the physician. Patients should be instructed on ways to facilitate faithful compliance with the dosage regimen throughout the usual long term of therapy, and on temporary doses reduction if episodes of diarrhea occur.

Drug Interactions

Bile acid sequestering agents, such as cholestyramine and colestipol, may interfere with the action of Chenodiol by reducing its absorption. Aluminum-based antacids have been shown to absorb bile acids in vitro and may be expected to interfere with Chenodiol in the same manner as the sequestering agents. Estrogen, oral contraceptive and collaborate (and perhaps other lipid-lowering drugs) increase biliary cholesterol secretion, and the incidence of cholesterol gallstones hence may counteract the effectiveness of Chenodiol.

Due to its hepatotoxicity, chenodiol can affect the pharmacodynamics of coumarin and its derivatives, causing unexpected prolongation of the prothrombin time and hemorrahages. Patients on concommitant therapy with chenodiol and coumarin or its derivatives should be monitored carefully. If prolongation of prothrombin time is observed, the coumarin dosage should be readjusted to give a prothrombin time 1½ to 2 times normal. If necessary chenodiol should be discontinued

Carcinogenesis, Mutagenesis, Impairment of Fertility

A two-year oral study of chenodiol in rats failed to show a carcinogenic potential at the tested levels of 15 to 60 mg/kg/day (1 to 4 times the maximum recommended human dose, MRHD). It has been reported that chenodiol given in long-term studies at oral doses up to 600 mg/kg/day (40 times the MRHD) to rats and 1000 mg/kg/day (65 times the MRHD) to mice induced benign and malignant liver cell tumors in female rats and cholangiomata in female rats and male mice. Two-year studies of lithocholic acid (a major metabolite of chenodiol) in mice (125 to 250 mg/kg/day) and rats (250 and 500 mg/kg/day) found it not to be carcinogenic. The dietary administration of Lithocholic acid to chickens is reported to cause hepatic adenomatous hyperplasia.

Pregnancy

Pregnancy Category X: See CONTRAINDICATIONS.

Nursing Mothers

It is not known whether chenodiol is excreted in human mild. Because many drugs are excreted in human milk, caution should be exercised when chenodiol is administered to a nursing mother.

Pediatric Use

The safety and effectiveness of chenodiol in children have not been established.

ADVERSE REACTIONS

Hepatobiliary:Dose-related serum aminotransferase (mainly SGPT) elevations, usually not accompanied by rises in alkaline phosphatase or bilirubin, occurred in 30% or more of patients treated with the recommended dose of Chenodiol. In most cases, these elevations were minor (1 ½ to 3 times the upper limit of laboratory normal) and transient, returning to within the normal range within six months despite continued administration of the drug. In 2% to 3% of patients, SGPT levels rose to over three times the upper limit of laboratory normal, recurred on rechallenge with the drug, and required discontinuation of chenodiol treatment. Enzyme levels have returned to normal following withdrawal of chenodiol (see WARNINGS).

Morphologic studies of liver biopsies taken before and after 9 and 24 months of treatment with chenodiol have shown that 63% of the patients prior to chenodiol treatment had evidence of intrahepatic cholestasis. Almost all pretreatment patients had electron microscopic abnormalities. By the ninth month of treatment, reexamination of two-thirds of the patients showed an 89% incidence of the signs of intrahepatic cholestasis. Two of 89 patients at the ninth month had lithocholate-like lesions in the canalicular membrane, although there were not clinical enzyme abnormalities in the face of continued treatment and no change in Type 2 light microscopic parameters.

Increased Cholecystectomy Rate: NCGS patients with a history of biliary pain prior to treatment had higher cholecystectomy rates during the study if assigned to low dosage chenodiol (375 mg/day) than if assigned to either placebo or high dosage chenodiol (750 mg/day). The association with low dosage chenodiol though not clearly a causal one, suggests that patients unable to take higher doses of chenodiol may be at greater risk of cholecystectomy.

Gastrointestinal:Dose-related diarrhea has been encountered in 30% to 40% of chenodiol-treated patients and may occur at any time during treatment, but is most commonly encountered when treatment is initiated. Usually, the diarrhea is mild, translucent, well-tolerated and does not interfere with therapy. Dose reduction has been required in 10% to 15% of patients, and in a controlled trial about half of these required a permanent reduction in dose. Anti-diarrhea agents have proven useful in some patients.

Discontinuation of chenodiol because of failure to control diarrhea is to be expected in approximately 3% of patients treated. Steady epigastric pain with nausea typical of lithiasis (biliary colic) usually is easily distinguishable from the crampy abdominal pain of drug-induced diarrhea.

Other less frequent, gastrointestinal side effects reported include urgency, cramps, heartburn, constipation, nausea, and vomiting, anorexic, epigastric distress, dyspepsis, flatulence and nonspecific abdominal pain.

Serum Lipids:Serum total cholesterol and low-density lipoprotein (LDL) cholesterol may rise 10% or more during administration of chenodiol: no change has been seen in the high-density lipoprotein (HDL) fraction; small decreases in serum triglyceride levels for females have been reported.

Hematologic:Decreases in white cell count, never below 3000, have been noted in a few patients treated with chenodiol; the drug was continued in all patients without incident.

DRUG ABUSE AND DEPENDENCE

Overdosage

Accidental or intentional overdoses of chenodiol have not been reported. One patient tolerated 4 gm/day (58 mg/kg/day) for six months without incident.

DOSAGE AND ADMINISTRATION

The recommended dose range for Chenodiol is 13 to 16 mg/kg/day in two divided doses, morning and night, starting with 250 mg b.i.d. the first two weeks and increasing by 250 mg/day each week thereafter until the recommended or maximum tolerated dose is reached. If diarrhea occurs during dosage buildup or later in treatment, it usually can be controlled by temporary dosage adjustment until symptoms abate, after which the previous dosage usually is tolerated. Dosage less than 10 mg/kg usually is ineffective and may be associated with increased risk of cholecystectomy, so is not recommended.

Body Weight |  | Recommended Tablets/Day | Dose Range mg/kg
lb | kg
100-130 | 45-58 | 3 | 17-13
131-185 | 59-75 | 4 | 17-13
186-200 | 76-90 | 5 | 18-14
201-235 | 91-107 | 6 | 18-14
236-275 | 108-125 | 7 | 18-14

The optimal frequency of monitoring liver function tests is not known. It is suggested that serum aminotransferase levels should be monitored monthly for the first three months and every three months thereafter during Chenodiol administration. Under NCGS guidelines, if a minor, usually transient elevations (1 ½ to3 three times the upper limit of normal) persisted longer than three to six months. Chenodiol was discontinued and resumed only after the aminotransferase level returned to normal; however, allowing the elevations to persist over such an interval is not know to be safe. Elevations over three times the upper limit of normal require immediate discontinuation of Chenodiol and usually reoccur on challenge.

Serum cholesterol should be monitored at six months intervals. It may be advisable to discontinue Chenodiol if cholesterol rises above the acceptable age-adjusted limit for given patient.

Oral cholecystograms or ultrasonograms are recommend at six to nine month intervals to monitor response. Complete dissolutions should be confirmed by a repeat test after one to three months continued Chenodiol administration. Most patients who eventually achieve complete dissolution will show partial (or complete) dissolution at the first on-treatment test. If partial dissolution is not seen by nine to 12 months, the likelihood of success of treating loner is greatly reduced; Chenodiol should be discontinued if there is no response by 18 months. Safety of use beyond 24 months is not established.

Stone recurrence can be expected within five years in 50% of cases. After confirmed dissolution, treatment generally should be stopped. Serial cholecystograms or ultrasonograms are recommended to monitor for recurrence, keeping in mind that radiolucency and gallbladder function should be established before starting another course of Chenodiol. A prophylactic doses is not established; reduced doses cannot be recommended; stones have recurred on 500 mg/day. Low cholesterol or carbohydrate diets, and dietary bran, have been reported to reduce biliary cholesterol; maintenance of reduced weight is recommended to forestall stone recurrence.

HOW SUPPLIED

Chenodal® (chenodiol tablets) is available as white film-coated 250 mg tablets imprinted “MP” on one side and "250" on the other in bottles of 100, NDC 68974-876-40.

Store at 20oC to 25oC (68oF to 77oF) [see USP Controlled Room Temperature].

Dispense in a tight container.

Manufactured for:
Retrophin, Inc.
San Diego, CA 92130
866-758-7068

Rev. 06/15

PRINCIPAL DISPLAY PANEL

NDC 68974-876-40
Chenodal
250 mg
100 Tablets
Rx Only